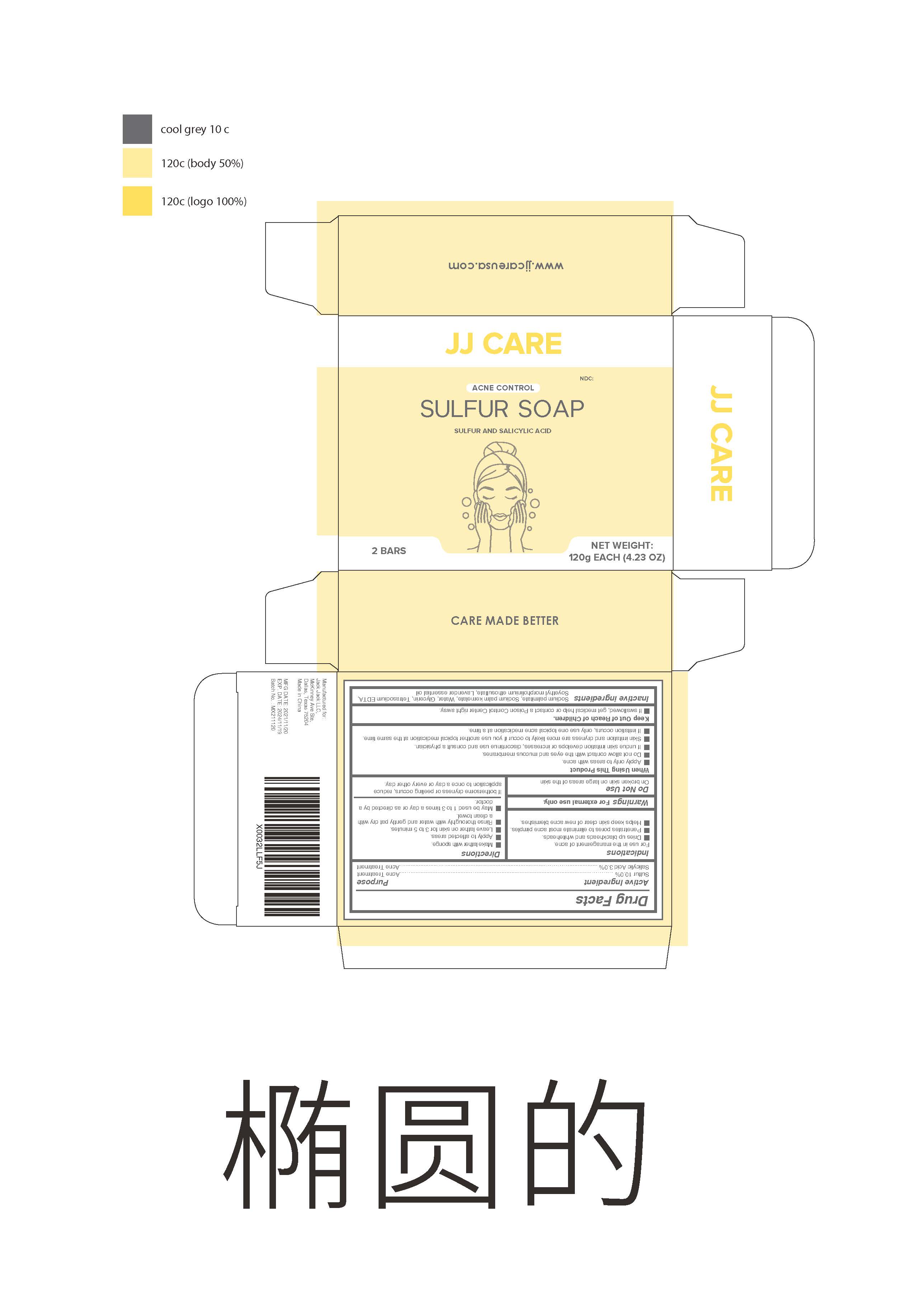 DRUG LABEL: Sulfur
NDC: 78565-106 | Form: SOAP
Manufacturer: Meixin Beauty & Health Care Products Co., Ltd.
Category: otc | Type: HUMAN OTC DRUG LABEL
Date: 20220402

ACTIVE INGREDIENTS: SALICYLIC ACID 3 g/100 g; SULFUR 10 g/100 g
INACTIVE INGREDIENTS: LAVENDER OIL; SOYETHYL MORPHOLINIUM ETHOSULFATE; WATER; EDETATE SODIUM; SODIUM PALMITATE; SODIUM PALM KERNELATE; GLYCERIN

78565-106
Sulfur soap

Active Ingredient

Sulfur10.0% ，Salicylic Acid3.0%

Purpose

Acne Treatment

Warnings

For external use only

Do not use

On broken skin on large areas of the skin

When Using This Product

Apply only to areas with acne.

Do not allow contact with the eyes and mucous membranes.

If undue skin irritation develops or increases , discontinue use and consult a physician.

Skin irritation and dryness are more likely to occur if you use another topical medication at the same time.

If irritation occurs , only use one topical acne medication at a time.

STOP USE

If undue skin irritation develops or increases , discontinue use and consult a physician.

Keep Out of Reach of Children.

If swallowed , get medical help or contact a Poison Control Center right away.

Directions

Make lather with sponge.

Apply to affected areas.

Leave lather on skin for 3 to 5 minutes.

Rinse thoroughly with water and gently pat dry with a clean toweI.

May be used 1 to 3 times a day or as directed by a doctor

Inactive ingredients

Sodium palmitate, Sodium palm kernelate, Water , Glycerin , Tetrasodium EDTA ,Soyethyl morpholinium ethosulfate , Lavender essential oil

Indications

For use in the management of acne.

Dries up blackheads and whiteheads.

Penetrates pores to eliminate most acne pimples.

Helps keep skin clear of new acne blemishes

Directions

Make lather with sponge.

Apply to affected areas.

Leave lather on skin for 3 to 5 minutes.

Rinse thoroughly with water and gently pat dry with a clean toweI.

May be used 1 to 3 times a day or as directed by a doctor

Package Label - Principal Display Panel

120g 78565-106-01